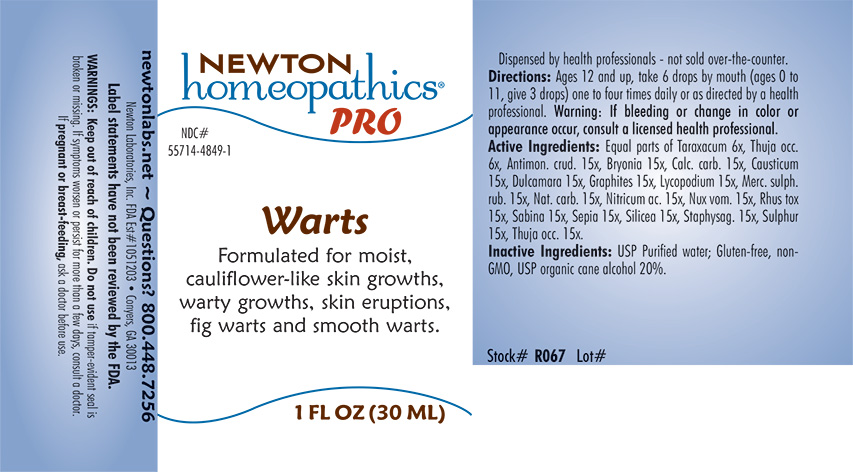 DRUG LABEL: Warts
NDC: 55714-4849 | Form: LIQUID
Manufacturer: Newton Laboratories, Inc.
Category: homeopathic | Type: HUMAN OTC DRUG LABEL
Date: 20221219

ACTIVE INGREDIENTS: ANTIMONY TRISULFIDE 15 [hp_X]/1 mL; BRYONIA ALBA ROOT 15 [hp_X]/1 mL; OYSTER SHELL CALCIUM CARBONATE, CRUDE 15 [hp_X]/1 mL; CAUSTICUM 15 [hp_X]/1 mL; SOLANUM DULCAMARA TOP 15 [hp_X]/1 mL; GRAPHITE 15 [hp_X]/1 mL; LYCOPODIUM CLAVATUM SPORE 15 [hp_X]/1 mL; MERCURIC SULFIDE 15 [hp_X]/1 mL; SODIUM CARBONATE 15 [hp_X]/1 mL; NITRIC ACID 15 [hp_X]/1 mL; STRYCHNOS NUX-VOMICA SEED 15 [hp_X]/1 mL; TOXICODENDRON PUBESCENS LEAF 15 [hp_X]/1 mL; JUNIPERUS SABINA LEAFY TWIG 15 [hp_X]/1 mL; SEPIA OFFICINALIS JUICE 15 [hp_X]/1 mL; SILICON DIOXIDE 15 [hp_X]/1 mL; DELPHINIUM STAPHISAGRIA SEED 15 [hp_X]/1 mL; SULFUR 15 [hp_X]/1 mL; THUJA OCCIDENTALIS LEAFY TWIG 15 [hp_X]/1 mL; TARAXACUM OFFICINALE 6 [hp_X]/1 mL
INACTIVE INGREDIENTS: ALCOHOL; WATER

Warts 4849L

INDICATIONS & USAGE SECTION

Formulated for moist, cauliflower-like skin growths, warty growths, skin eruptions, fig warts and smooth warts.

DOSAGE & ADMINISTRATION SECTION

Directions: Ages 12 and up, take 6 drops by mouth (ages 0 to 11, give 3 drops) one to four times daily or as directed by a health professional. WARNING: If bleeding or change in color or appearance occur, consult a licensed health professional.

OTC - ACTIVE INGREDIENT SECTION

Equal parts of Taraxacum 6x, Thuja occ. 6x. Antimon. crud. 15x, Bryonia 15x, Calc.carb. 15x, Causticum 15x, Dulcamara 15x, Graphites 15x, Lycopodium 15x, Merc. sulph. rub. 15x, Nat. carb. 15x, Nitricum ac.15x, Nux vom. 15x, Rhus tox 15x, Sabina 15x, Sepia 15x, Silicea 15x, Staphysag. 15x, Sulphur 15x, Thuja occ. 15x.

OTC - PURPOSE SECTION

Formulated for moist, cauliflower-like skin growths, warty growths, skin eruptions, fig warts and smooth warts.

INACTIVE INGREDIENT SECTION

Inactive Ingredients: USP Purified Water; USP Gluten-free, non-GMO, organic cane alcohol 20%.

QUESTIONS SECTION

newtonlabs.net ~ Questions? 800.448.7256

Newton Laboratories, Inc. FDA Est # 1051203 - Conyers, GA 30013

WARNINGS SECTION

WARNINGS: If bleeding or change in color or appearance occur, consult a licensed health professional.

WARNINGS: Keep out of reach of children. Do not use if tamper-evident seal is broken or missing. If symptoms worsen or persist for more than a few days, consult a doctor. If pregnant or breast-feeding, ask a doctor before use.

OTC - PREGNANCY OR BREAST FEEDING SECTION

If pregnant or breast-feeding, ask a doctor before use.

OTC - KEEP OUT OF REACH OF CHILDREN SECTION

Keep out of reach of children.